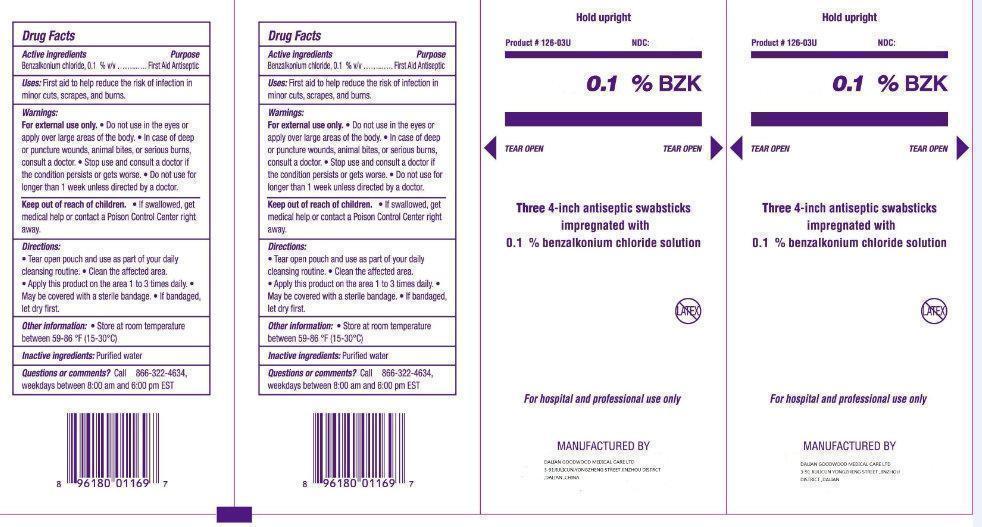 DRUG LABEL: BZK
NDC: 50685-010 | Form: SWAB
Manufacturer: Dalian Goodwood Medical Care Ltd.
Category: otc | Type: HUMAN OTC DRUG LABEL
Date: 20230525

ACTIVE INGREDIENTS: BENZALKONIUM CHLORIDE 1 mg/1 g
INACTIVE INGREDIENTS: WATER

0.1% BZK Swabstick

Active Ingredients

Benzalkonium chloride, 0.1 %

Purpose

First Aid Antiseptic

Uses

First aid to help reduce the risk of infection in minor cuts, scrapes, and burns.

Warnings

For external use only.

- Do not use in the eyes or apply over large areas of the body.
- In case of deep or puncture wounds, animal bites, or serious burns, consult a doctor.

Stop use and consult a doctor

if the condition persists or gets worse.

Do not use

for longer than 1 week unless directed by a doctor.

Keep out of reach of children

If swallowed, get medical help or contact a Poison Control Center right away.

Directions

- Tear open pouch and use as part of your daily cleansing routine.
- Chean the affected area.
- Apply this product on the area 1 to 3 times daily.
- May be covered with a sterile bandage.
- If bandaged, let dry first.

Other information

Store at room temperature between 59-86 F (15-30 C)

Inactive ingredients

Purified water

Questions or comments?

Call 866-322-4634,

weekdays between 8:00 am and 6:00 pm EST